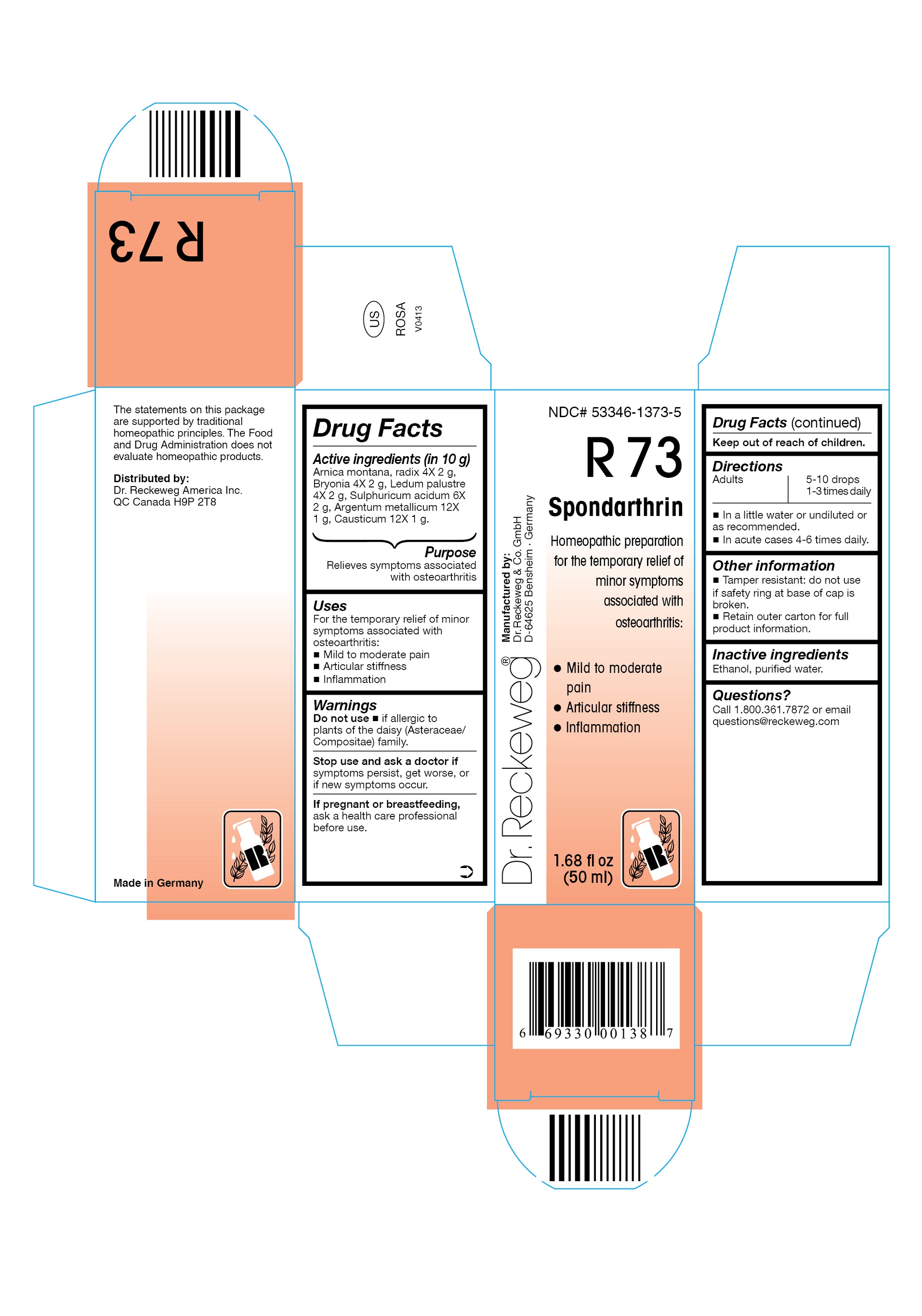 DRUG LABEL: DR. RECKEWEG R73 Spondarthrin
NDC: 53346-1373 | Form: LIQUID
Manufacturer: PHARMAZEUTISCHE FABRIK DR. RECKEWEG & CO
Category: homeopathic | Type: HUMAN OTC DRUG LABEL
Date: 20130403

ACTIVE INGREDIENTS: ARNICA MONTANA ROOT 4 [hp_X]/50 mL; BRYONIA DIOICA ROOT 4 [hp_X]/50 mL; LEDUM PALUSTRE TWIG  4 [hp_X]/50 mL; SULFURIC ACID 6 [hp_X]/50 mL; SILVER 12 [hp_X]/50 mL; CAUSTICUM 12 [hp_X]/50 mL
INACTIVE INGREDIENTS: ALCOHOL; WATER

DR. RECKEWEG R73 Spondarthrin

Active ingredients

Arnica montana, radix 4X 2 g, Bryonia 4X 2 g, Ledum palustre 4X 2 g, Sulphuricum acidum 6X 2 g, Argentum metallicum 12X 1 g, Causticum 12X 1 g in 10 g.

Purpose

Relieves symptoms associated with osteoarthritis

Uses

For the temporary relief of minor symptoms associated with osteoarthritis:

- Mild to moderate pain
- Articular stiffness
- Inflammation

Warnings

Do not use

- if allergic to plants of the daisy (Asteraceae/Compositae) family.

Stop use and ask a doctor if symptoms persist, get worse, or if new symptoms occur.

PREGNANCY OR BREAST FEEDING

If pregnant or breastfeeding, ask a health care professional before use.

Keep out of reach of children.

Directions
Adults 5-10 drops 1-3 times daily; in acute cases: 4-6 times daily in a little water or undiluted or as recommended.

Other information

- Tamper resistant: do not use if safety ring at base of cap is broken.
- Retain outer carton for full product information.

Inactive ingredients

Ethanol, purified water.

Questions?

Call 1-800-361-7872 or email questions@reckeweg.com

PACKAGE LABEL

NDC# 53346-1373-5

Dr. Reckeweg R73 Spondarthrin

Homeopathic preparation for the temporary relief of minor symptoms associated with osteoarthritis:

- Mild to moderate pain
- Articular stiffness
- Inflammation

Manufactured by:

Dr. Reckeweg Co. GmbH

D-64625 Bensheim

Germany

1.68 fl oz
(50 ml)